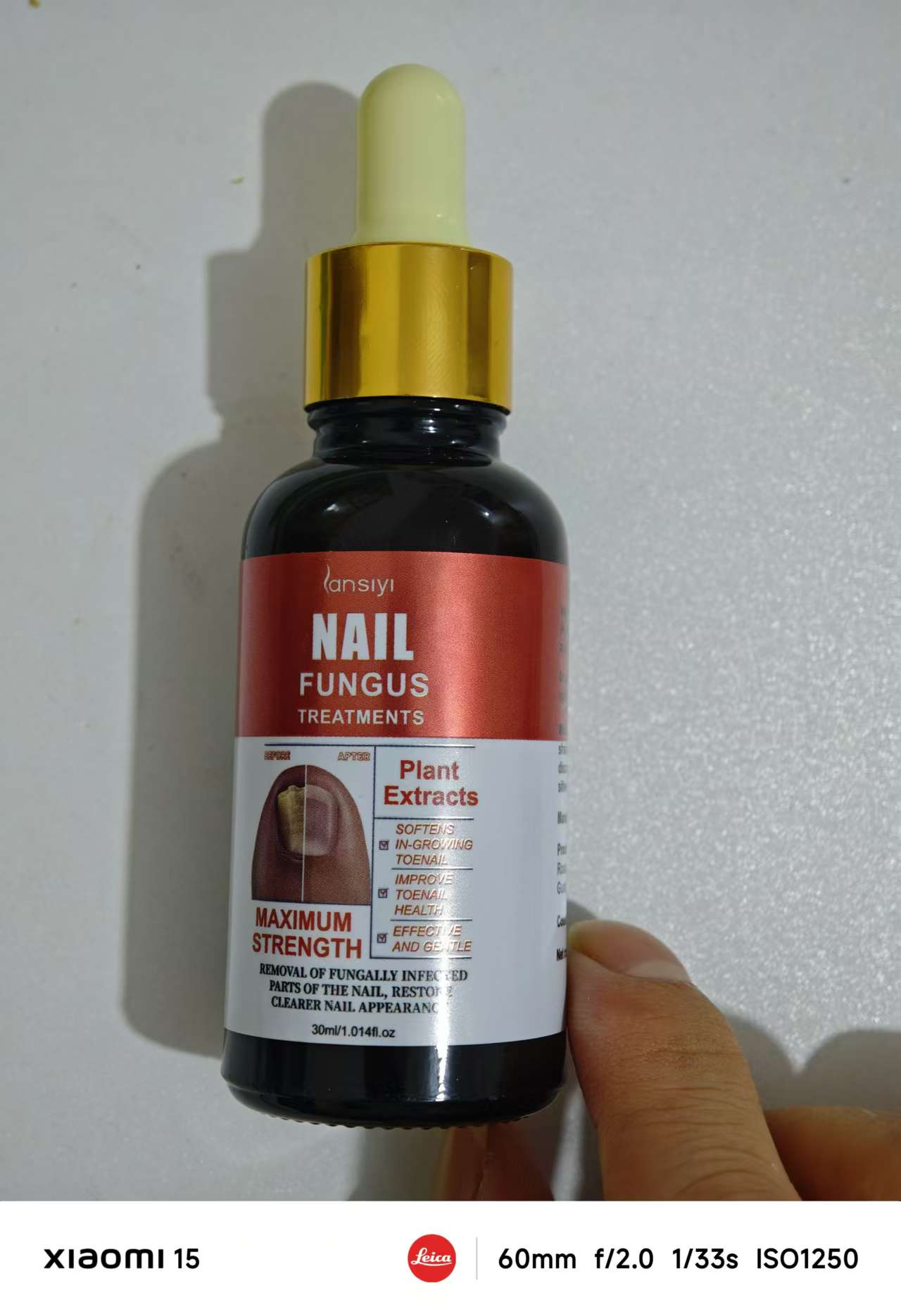 DRUG LABEL: Nall fungus treatments
NDC: 84727-005 | Form: LIQUID
Manufacturer: Guangzhou Baishili Trading Co., Ltd
Category: otc | Type: HUMAN OTC DRUG LABEL
Date: 20241110

ACTIVE INGREDIENTS: (2-AMINO-5,6-DICHLOROQUINAZOLIN-3(4H )-YL)ACETIC ACID 0.8 g/0.8 mL; REHMANNIA CHINENSIS ROOT EXTRACT 0.8 g/0.8 mL
INACTIVE INGREDIENTS: AQUA

Health care function

Nail fungus treatments aim to address fungal infections in the nails, providing benefits such as:

Eliminating Fungal Infection: The primary goal is to kill the fungus causing the infection and prevent it from spreading to other nails or skin areas.

Reducing Discoloration: Many treatments help reduce yellowing or discoloration, restoring the nail’s natural color over time.

Improving Nail Texture: Treatments can help smooth out thickened or brittle nails, making them look and feel healthier.

Preventing Recurrence: Some treatments strengthen the nail and surrounding area to prevent future infections.

Relieving Symptoms: Nail fungus treatments can alleviate symptoms like itching, inflammation, and pain caused by the infection.

Promoting Healthy Nail Growth: Effective treatments support healthy nail regrowth, replacing infected areas with clearer, stronger nails.

Results vary depending on the severity of the infection and consistency of treatment, with noticeable improvements often taking a few weeks to several months.

Usage

Nail fungus treatments are typically used as follows:

Clean the Affected Area: Wash and dry the infected nail and surrounding skin thoroughly before applying the treatment.

Trim and File the Nail: Trim the infected nail as short as possible, and gently file any thickened areas. This helps the treatment penetrate better.

Apply the Treatment: Follow the product instructions carefully. Some treatments are applied directly to the nail and surrounding skin, while others may need to be brushed or sprayed.

Allow to Dry Completely: Let the treatment dry fully to ensure maximum effectiveness and avoid spreading the fungus.

Use Consistently: Apply the treatment regularly, as directed (e.g., once or twice daily), for the best results. Fungal infections can take several months to fully heal, so consistency is key.

Maintain Nail Hygiene: Keep nails clean and dry, and avoid tight, non-breathable shoes or socks to help prevent reinfection.

For best results, follow the product's specific instructions closely, as different treatments may have unique guidelines.

WARNINGS

Here are some important warnings to keep in mind when using nail fungus treatments:

Avoid Contact with Eyes and Mucous Membranes: Do not allow the treatment to come into contact with eyes, mouth, or other mucous membranes. Rinse thoroughly with water if accidental contact occurs.

Do Not Apply to Broken or Irritated Skin: Avoid applying the treatment to cuts, scrapes, or areas with skin irritation, as this can cause further discomfort or infection.

Consult a Doctor if Pregnant, Nursing, or Taking Medications: Some ingredients in nail fungus treatments may not be suitable for everyone. Consult a healthcare professional before using if you are pregnant, nursing, or taking any medications.

Discontinue Use if Irritation Occurs: If you experience redness, swelling, itching, or burning, stop using the treatment immediately and consult a healthcare provider.

Not for Use in Children without Medical Advice: Nail fungus treatments may not be safe for young children. Consult a doctor before use in pediatric cases.

Keep Out of Reach of Children: Store the product in a safe place where children cannot access it.

Avoid Flammable Conditions: Many treatments contain alcohol or other flammable substances. Use away from open flames or heat sources.

Following these warnings can help ensure the safe and effective use of nail fungus treatments.

STOP USE

Here are the "Stop Use" instructions for OTC (Over-the-Counter) nail fungus treatments:

Allergic Reaction: If you experience a severe allergic reaction, such as rash, swelling, itching, or blisters, stop using the product immediately and consult a doctor.

Increased Skin Irritation or Discomfort: If you experience burning, stinging, or increased irritation during use, discontinue use to avoid further skin irritation or damage.

Symptoms Not Improving or Worsening: If your symptoms do not improve after several weeks of use, or if they worsen, stop using the product and seek medical advice, as stronger treatment may be required.

Infection Spreading: If the fungal infection spreads to other nails, fingers, or skin, discontinue use immediately and consult a doctor for more effective treatment options.

Unusual Side Effects: If you experience any side effects not listed in the instructions, stop using the product and seek medical attention.

If any of these issues occur, it is important to stop using the OTC nail fungus treatment to avoid worsening the condition and to receive proper medical treatment.

KEEP OUT OF REACH OF CHILDREN

Here’s the "Keep Out of Reach of Children" section for OTC (Over-the-Counter) nail fungus treatments:

Keep Out of Reach of Children:

Risk of Accidental Ingestion: Some nail fungus treatments may be harmful if swallowed. Keep the product tightly closed and stored in a safe place where children cannot reach it.

Ingestion or Skin Contact Warning: If the product is ingested or comes into contact with a child's skin or eyes, seek medical attention immediately. Follow the first aid instructions on the label.

Child Safety: For safety, ensure that children cannot access the product, and never allow children to use it without adult supervision.

It's crucial to store the product in a secure location to prevent accidental ingestion or misuse, ensuring the safety of children.

DOSAGE AND ADMINISTRATION

Here’s the Dosage & Administration section for OTC (Over-the-Counter) nail fungus treatments:

Dosage & Administration:

Clean the Affected Area: Wash and dry the infected nail and surrounding skin thoroughly before applying the treatment.

Apply the Treatment: Follow the instructions on the product label. Typically, apply a thin layer of the treatment to the affected nail(s) and surrounding skin once or twice daily.

Allow the Product to Dry: After applying, let the treatment dry completely to ensure maximum effectiveness.

Regular Application: For best results, use the product consistently as directed. Continue applying until the infection clears up, which may take several weeks or months depending on the severity.

Avoid Covering the Nail: Do not cover the treated nail with a bandage or tight covering unless specifically instructed by a healthcare provider, as the product may need to air dry.

Do Not Skip Doses: Apply the treatment regularly as directed, even if the symptoms improve, to prevent recurrence of the infection.

Consult a Doctor if Symptoms Persist: If symptoms do not improve after several weeks or if the infection worsens, stop using the product and consult a healthcare professional.

Ensure that you follow the specific dosage instructions provided with the product you are using for optimal results.

INACTIVE INGREDIENT

Aqua

DOSAGE AND ADMINISTRATION

Acetic Acid
Rehmannia Chinensis Root Extract